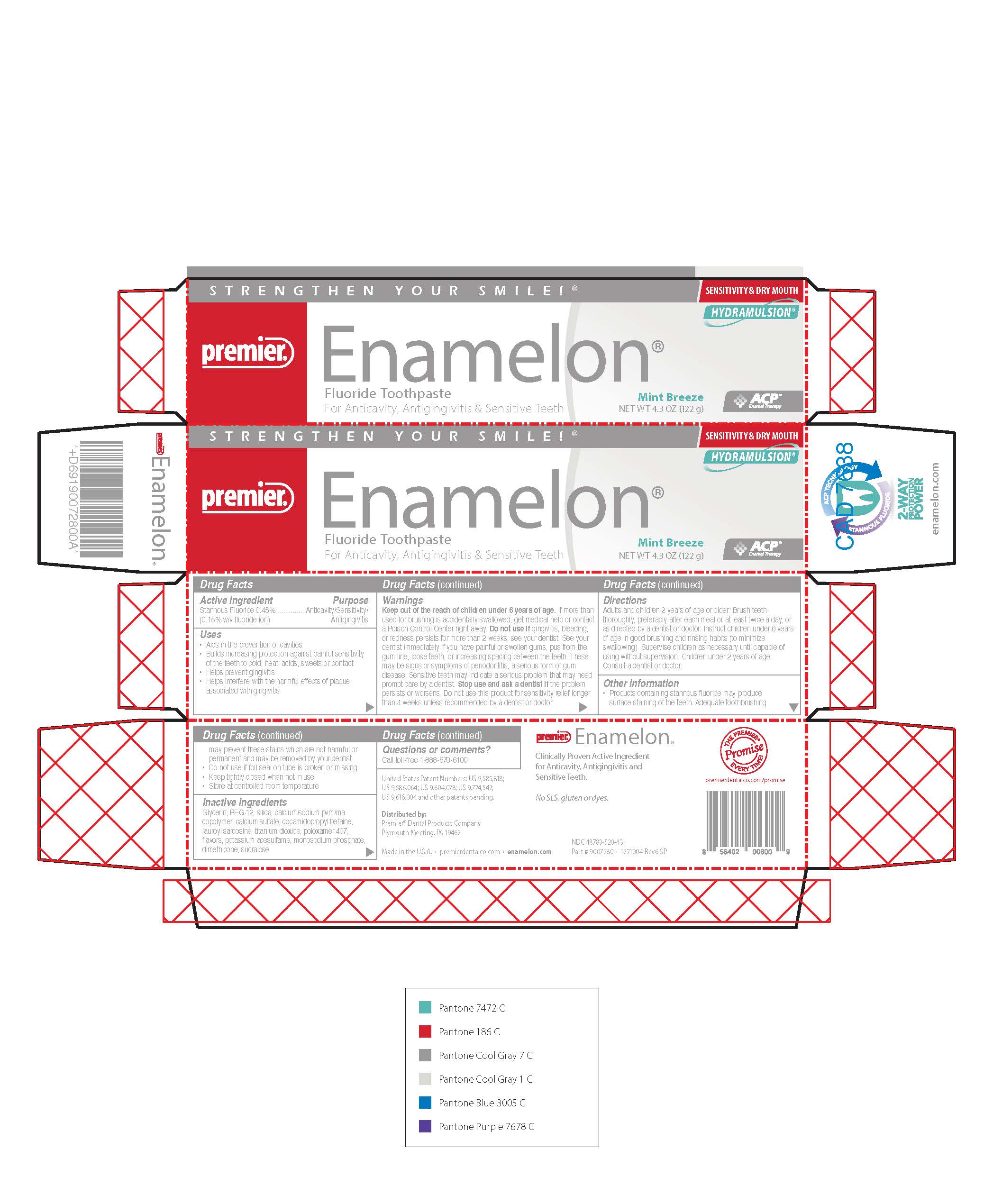 DRUG LABEL: Enamelon
NDC: 48783-520 | Form: PASTE, DENTIFRICE
Manufacturer: Premier Dental Products Company
Category: otc | Type: HUMAN OTC DRUG LABEL
Date: 20260113

ACTIVE INGREDIENTS: STANNOUS FLUORIDE 0.00454 g/1 g
INACTIVE INGREDIENTS: GLYCERIN; POLYETHYLENE GLYCOL, UNSPECIFIED; SILICON DIOXIDE; CALCIUM/SODIUM MALEATE METHYL VINYL ETHER COPOLYMER (1000000 MW, 1900 MPA.S AT 11%); COCAMIDOPROPYL BETAINE; CALCIUM SULFATE; POLOXAMER 407; DIMETHICONE; LAUROYL SARCOSINE; TITANIUM DIOXIDE; ACESULFAME POTASSIUM; SODIUM PHOSPHATE, MONOBASIC; SUCRALOSE

Enamelon Paste

Active ingredient

Stannous fluoride 0.45% (0.16% w/v fluoride ion)

Purpose

Anticavity/Sensitivity Relief/Antigingivitis

Uses

- Aids in the prevention of cavities
- Builds increasing protection against painful sensitivity of the teeth to cold, heat, acids, sweets or contact
- Helps prevent gingivitis
- Helps interfere with the harmful effects of plaque associated with gingivitis

Warnings

Keep out of the reach of children under 6 years of age.

WARNINGS

If more than used for brushing is accidentally swallowed, get medical help or contact a Poison Control Center right away. Do not use if gingivitis, bleeding, or redness persists for more than 2 weeks, see your dentist. See your dentist immediately if you have painful or swollen gums, pus from the gum line, loose teeth, or increasing spacing between the teeth. These may be signs or symptoms of periodontitis, a serious form of gum disease. Sensitive teeth may indicate a serious problem that may need prompt care by a dentist. Stop use and ask a dentist if the problem persists or worsens. Do not use this product for sensitivity relief longer than 4 weeks unless recommended by a dentist or doctor.

Directions

Adults and children 2 years of age or older: Brush teeth thoroughly, preferably after each meal or at least twice a day, or as directed by a dentist or doctor. Instruct children under 6 years of age in good brushing and rinsing habits (to minimize swallowing). Supervise children as necessary until capable of using without supervision. Children under 2 years of age: Consult a dentist or doctor.

Other information

- Products containing stannous fluoride may produce surface staining of the teeth. Adequate toothbrushing may prevent these stains which are not harmful or permanent and may be removed by your dentist.
- Do not use if foil seal on tube is broken or missing
- Keep tightly closed when not in use
- Store at controlled room temperature

Inactive ingredients

Glycerin, polyethylene glycol, silica, calcium/sodium maleate methyl vinyl ether copolymer, cocamidopropyl betaine, calcium sulfate, poloxamer 407, dimethicone, lauroyl-sarcosine, titanium dioxide, flavor, acesulfame k, monosodium phosphate, sucralose

Questions or comments?

Call toll-free 1-888-670-6100

Monday-Thursday 8am-5pm EST, Friday 8am-4pm EST

Distributed By

Premier® Dental Products Company, Plymouth Meeting, PA 19462

www.premusa.com Part # 9007280 www.enamelon.com

United States Patent Numbers : US 5,993,784, US 5,711,936, US 5,651,959 and other patents pending. Made in U.S.A.

Ultramulsion® is a registered trademark of WhiteHill Oral Technologies, Inc.

PRINCIPAL DISPLAY PANEL

STRENGTHEN YOUR SMILE!

ACPTM Enamel Therapy

Premier®

Enamelon®

Mint Breeze

Fluoride Toothpaste NET WT 4.3 OZ (122 g)

For Anticavity, Antigingivitis & Sensitive Teeth

HYDRAMULSION®

NDC 48783-520-43